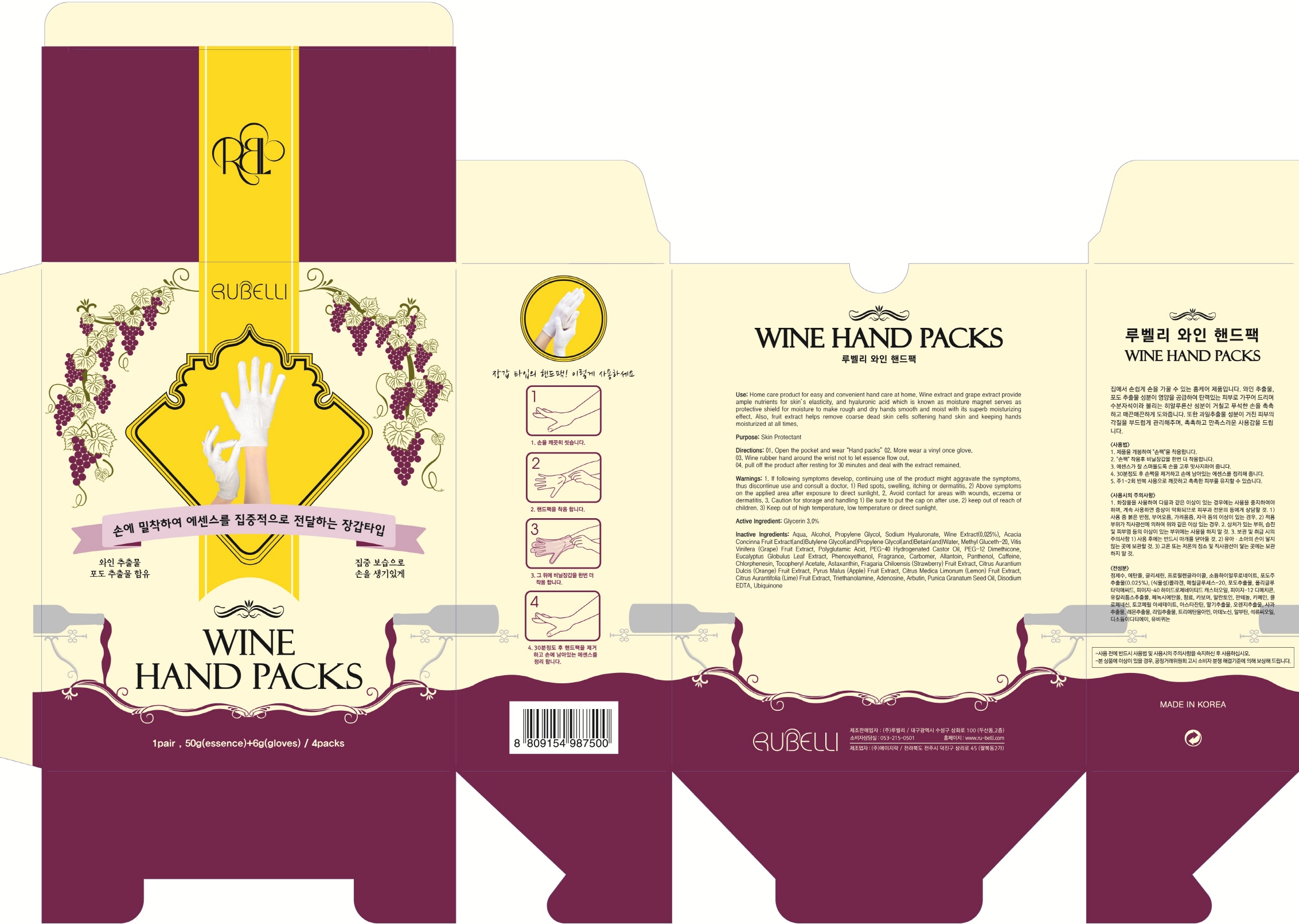 DRUG LABEL: Rubelli Wine Hand Packs
NDC: 71006-020 | Form: PATCH
Manufacturer: RUBELLI CO.,LTD
Category: otc | Type: HUMAN OTC DRUG LABEL
Date: 20161011

ACTIVE INGREDIENTS: Glycerin 1.50 g/50 g
INACTIVE INGREDIENTS: WATER; Alcohol

ACTIVE INGREDIENT

Active Ingredient: Glycerin 3.0%

INACTIVE INGREDIENT

Inactive Ingredients: Aqua, Alcohol, Propylene Glycol, Sodium Hyaluronate, Wine Extract(0.025%), Acacia Concinna Fruit Extract(and)Butylene Glycol(and)Propylene Glycol(and)Betain(and)Water, Methyl Gluceth-20, Vitis Vinifera (Grape) Fruit Extract, Polyglutamic Acid, PEG-40 Hydrogenated Castor Oil, PEG-12 Dimethicone, Eucalyptus Globulus Leaf Extract, Phenoxyethanol, Fragrance, Carbomer, Allantoin, Panthenol, Caffeine, Chlorphenesin, Tocopheryl Acetate, Astaxanthin, Fragaria Chiloensis (Strawberry) Fruit Extract, Citrus Aurantium Dulcis (Orange) Fruit Extract, Pyrus Malus (Apple) Fruit Extract, Citrus Medica Limonum (Lemon) Fruit Extract, Citrus Aurantifolia (Lime) Fruit Extract, Triethanolamine, Adenosine, Arbutin, Punica Granatum Seed Oil, Disodium EDTA, Ubiquinone

PURPOSE

Purpose: Skin Protectant

WARNINGS

1. If following symptoms develop, continuing use of the product might aggravate the symptoms, thus discontinue use and consult a doctor.

1)Red spots, swelling, itching or dermatitis. 2)Above symptoms on the applied area after exposure to direct sunlight.

2. Avoid contact for areas with wounds, eczema or dermatitis.

3.Caution for storage and handling

1) Be sure to put the cap on after use. 2) keep out of reach of children. 3) Keep out of high temperature, low temperature or direct sunlight.

KEEP OUT OF REACH OF CHILDREN

Use

Home care product for easy and convenient hand care at home. Wine extract and grape extract provide ample nutrients for skin’s elasticity, and hyaluronic acid which is known as moisture magnet serves as protective shield for moisture to make rough and dry hands smooth and moist with its superb moisturizing effect. Also, fruit extract helps remove coarse dead skin cells softening hand skin and keeping hands moisturized at all times.

Directions

01. Open the pocket and wear “Hand packs” 02. More wear a vinyl once glove. 03. Wine rubber hand around the wrist not to let essence flow out. 04. pull off the product after resting for 30 minutes and deal with the extract remained.